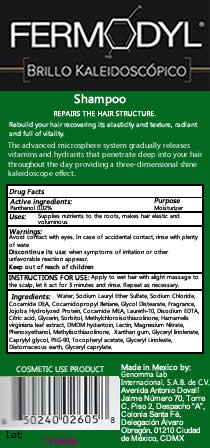 DRUG LABEL: FERMODYL
NDC: 51769-202 | Form: SHAMPOO
Manufacturer: All Natural Dynamics
Category: otc | Type: HUMAN OTC DRUG LABEL
Date: 20201219

FERMODYL BRILLO KALEIDOSCOPIO

Active Ingredients:

Pathenol 0.002 mL per 1 ML

Precautions:

Avoid contact with eyes. In case of accidental contact, rinse with plenty of water. Discontinue its use when symptoms of irritation or other unfavorable reaction appear.

Warning

Keep out of reach of children.

Purpose:

Repairs the Hair Structure

Indications:

For external use only

Inactive Ingredients:

Water, Sodium Lauryl Ether Sulfate, Sodium Chloride, Cocamide DEA, Cocamidopropyl Betiane, Glycol Distearate, Fragrance, Jojoba Hydrolyzed Protein, Cocamide MEA, Laureth-10, Disodium EDTA, Citric acid, Glycerin, Sorbitol, Methylchloroisothiazolinone, Hamamelis virginiana leaf extract, DMDM hydantoin, Lectin, Magnesium Nitrate, Phenoxyethanol, Methylisothiazolinone, Xanthan gum, Glyceryl linolenate, Caprylyl glycol, PEG-90, Tocopheryl acetate, Glyceryl Linoleate, Diatomaceous earth, Glyceryl caprylate.

Application:

Apply to wet hair with a light massage to the scalp, let it act for 3 minutes and rinse. Repeat as necessary.